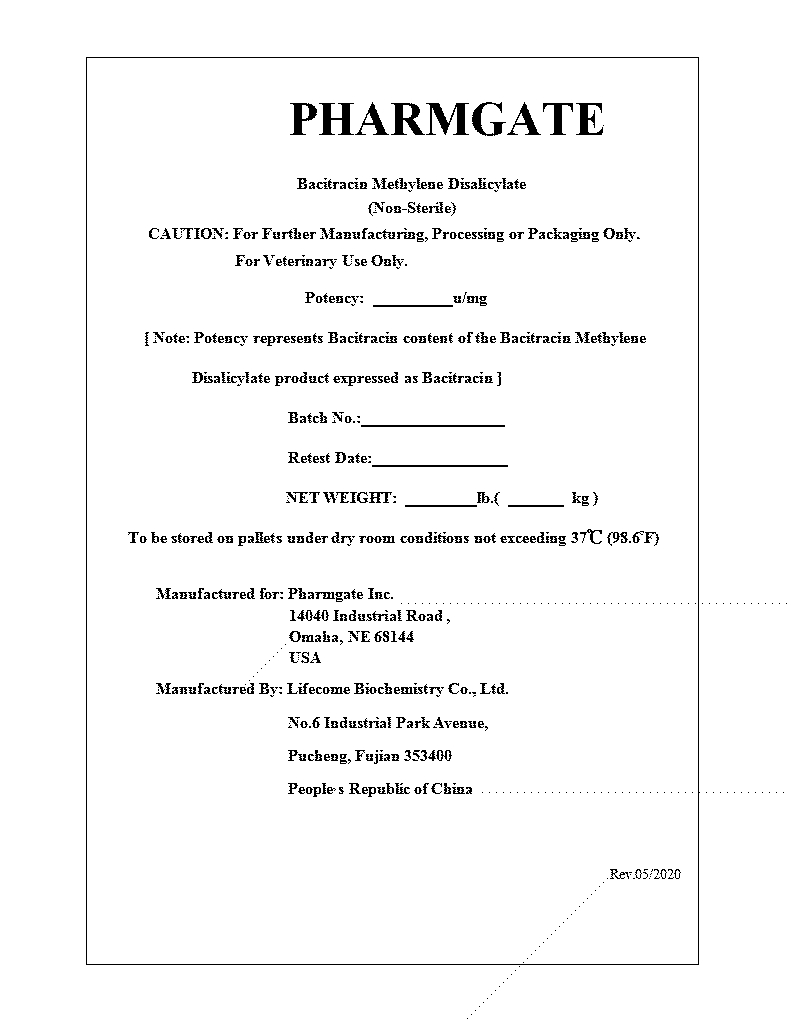 DRUG LABEL: Bacitracin Methylene Disalicylate Feed  Grade
NDC: 41699-0001 | Form: GRANULE
Manufacturer: Lifecome Biochemistry Co., Ltd
Category: other | Type: BULK INGREDIENT - ANIMAL DRUG
Date: 20230210

ACTIVE INGREDIENTS: BACITRACIN A METHYLENEDISALICYLATE 1 kg/1 kg

Bacitracin Methylene Disalicylate